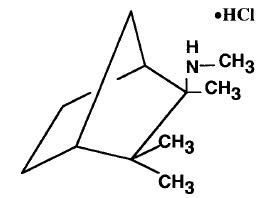 DRUG LABEL: Unknown
Manufacturer: Targacept, Inc.
Category: prescription | Type: HUMAN PRESCRIPTION DRUG LABEL
Date: 20080603

TABLETS
INVERSINE®
(MECAMYLAMINE HCl)

DESCRIPTION

INVERSINE® (Mecamylamine HCl) is a potent, oral antihypertension agent and ganglion blocker, and is a secondary amine. It is N,2,3,3-tetramethyl-bicyclo [2.2.1] heptan- 2 -amine hydrochloride. Its empirical formula is C11H21N • HCl and its structural formula is:

It is a white, odorless, or practically odorless, crystalline powder, is highly stable, soluble in water and has a molecular weight of 203.75.

INVERSINE is supplied as tablets for oral use, each containing 2.5 mg mecamylamine HCl. Inactive ingredients are acacia, calcium phosphate, D&C Yellow 10, FD&C Yellow 6, lactose, magnesium stearate, starch, and talc.

CLINICAL PHARMACOLOGY

Mecamylamine reduces blood pressure in both normotensive and hypertensive individuals. It has a gradual onset of action (1/2 to 2 hours) and a longlasting effect (usually 6 to 12 hours or more). A small oral dosage often produces a smooth and predictable reduction of blood pressure. Although this antihypertensive effect is predominantly orthostatic, the supine blood pressure is also significantly reduced.

Pharmacokinetics and Metabolism

Mecamylamine is almost completely absorbed from the gastrointestinal tract, resulting in consistent lowering of blood pressure in most patients with hypertensive cardiovascular disease. Mecamylamine is excreted slowly in the urine in the unchanged form. The rate of its renal elimination is influenced markedly by urinary pH. Alkalinization of the urine reduces, and acidification promotes, renal excretion of mecamylamine.

Mecamylamine crosses the blood-brain and placental barriers.

INDICATIONS AND USAGE

For the management of moderately severe to severe essential hypertension and in uncomplicated cases of malignant hypertension.

CONTRAINDICATIONS

INVERSINE should not be used in mild, moderate, labile hypertension and may prove unsuitable in uncooperative patients. It is contraindicated in coronary insufficiency or recent myocardial infarction.

INVERSINE should be given with great discretion, if at all, when renal insufficiency is manifested by a rising or elevated BUN. The drug is contraindicated in uremia. Patients receiving antibiotics and sulfonamides should generally not be treated with ganglion blockers. Other contraindications are glaucoma, organic pyloric stenosis or hypersensitivity to the product.

WARNINGS

Mecamylamine, a secondary amine, readily penetrates into the brain and thus may produce central nervous system effects. Tremor, choreiform movements, mental aberrations, and convulsions may occur rarely. These have occurred most often when large doses of INVERSINE were used, especially in patients with cerebral or renal insufficiency.

When ganglion blockers or other potent antihypertensive drugs are discontinued suddenly, hypertensive levels return. In patients with malignant hypertension and others, this may occur abruptly and may cause fatal cerebral vascular accidents or acute congestive heart failure. When INVERSINE is withdrawn, this should be done gradually and other antihypertensive therapy usually must be substituted. On the other hand, the effects of INVERSINE sometimes may last from hours to days after therapy is discontinued.

PRECAUTIONS

General

The patient's condition should be evaluated carefully, particularly as to renal and cardiovascular function. When renal, cerebral, or coronary blood flow is deficient, any additional impairment, which might result from added hypotension, must be avoided. The use of INVERSINE in patients with marked cerebral and coronary arteriosclerosis or after a recent cerebral accident requires caution.

The action of INVERSINE may be potentiated by excessive heat, fever, infection, hemorrhage, pregnancy, anethesia, surgery, vigorous exercise, other antihypertensive drugs, alcohol, and salt depletion as a result of diminished intake or increased excretion due to diarrhea, vomiting, excessive sweating, or diuretics.

During therapy with INVERSINE, sodium intake should not be restricted but, if necessary, the dosage of the ganglion blocker must be adjusted.

Since urinary retention may occur in patients on ganglion blockers, caution is required in patients with prostatic hypertrophy, bladder neck obstruction, and urethral stricture.

Frequent loose bowel movements with abdominal distention and decreased borborygmi may be the first signs of paralytic ileus. If these are present, INVERSINE should be discontinued immediately and remedial steps taken.

Information for patients

INVERSINE may cause dizziness, lightheadedness, or fainting, especially when rising from a lying or sitting position. This effect may be increased by alcoholic beverages, exercise, or during hot weather. Getting up slowly may help alleviate such a reaction.

Drug Interactions

Patients receiving antibiotics and sulfonamides generally should not be treated with ganglion blockers.

The action of INVERSINE may be potentiated by anesthesia, other antihypertensive drugs and alcohol.

Carcinogenesis, Mutagenesis, Impairment of Fertility

Long-term studies in animals have not been performed to evaluate the effects upon fertility, mutagenic or carcinogenic potential of INVERSINE.

Pregnancy

Pregnancy Category C. Animal reproduction studies have not been conducted with INVERSINE. It is not known whether INVERSINE can cause fetal harm when given to a pregnant woman or can affect reproductive capacity. INVERSINE should be given to a pregnant woman only if clearly needed.

Nursing Mothers

Because of the potential for serious adverse reactions in nursing infants from INVERSINE, a decision should be made whether to discontinue nursing or to discontinue the drug, taking into account the importance of the drug to the mother.

Pediatric Use

Safety and effectiveness in pediatric patients have not been established.

ADVERSE REACTIONS

The following adverse reactions have been reported and within each category are listed in order of decreasing severity.

Gastrointestinal: Ileus, constipation (sometimes preceded by small, frequent liquid stools), vomiting, nausea, anorexia, glossitis and dryness of mouth.

Cardiovascular: Orthostatic dizziness and syncope, postural hypotension.

Nervous System/Psychiatric: Convulsions, choreiform movements, mental aberrations, tremor, and paresthesias (see WARNINGS).

Respiratory: Interstitial pulmonary edema and fibrosis.

Urogenital: Urinary retention, impotence, decreased libido.

Special Senses: Blurred vision, dilated pupils.

Miscellaneous: Weakness, fatigue, sedation.

OVERDOSAGE

Signs of overdosage include: hypotension (which may progress to peripheral vascular collapse), postural hypotension, nausea, vomiting, diarrhea, constipation, paralytic ileus, urinary retention, dizziness, anxiety, dry mouth, mydriasis, blurred vision, or palpitations. A rise in intraocular pressure may occur.

Pressor amines may be used to counteract excessive hypotension. Since patients being treated with ganglion blockers are more than normally reactive to pressor amines, small doses of the latter are recommended to avoid excessive response.

The oral LD50 of mecamylamine in the mouse is 92 mg/kg.

DOSAGE AND ADMINISTRATION

Therapy is usually started with one 2.5 mg tablet of INVERSINE twice a day. This initial dosage should be modified by increments of one 2.5 mg tablet at intervals of not less than 2 days until the desired blood pressure response occurs (the criterion being a dosage just under that which causes signs of mild postural hypotension).

The average total daily dosage of INVERSINE is 25 mg, usually in three divided doses. However, as little as 2.5 mg daily may be sufficient to control hypertension in some patients. A range of two to four or even more doses may be required in severe cases when smooth control is difficult to obtain. In severe or urgent cases, larger increments at smaller intervals may be needed. Partial tolerance may develop in certain patients, requiring an increase in the daily dosage of INVERSINE.

Administration of INVERSINE after meals may cause a more gradual absorption and smoother control of excessively high blood pressure. The timing of doses in relation to meals should be consistent. Since the blood pressure response to antihypertensive drugs is increased in the early morning, the larger dose should be given at noontime and perhaps in the evening. The morning dose, as a rule, should be relatively small and in some instances may even be omitted.

The initial regulation of dosage should be determined by blood pressure readings in the erect position at the time of maximal effect of the drug, as well as by other signs and symptoms of orthostatic hypotension.

The effective maintenance dosage should be regulated by blood pressure readings in the erect position and by limitation of dosage to that which causes slight faintness or dizziness in this position. If the patient or a relative can use a sphygmomanometer, instructions may be given to reduce or omit a dose if readings fall below a designated level or if faintness or lightheadedness occurs. However, no change should be instituted without the knowledge of the physician.

Close supervision and education of the patient, as well as critical adjustment of dosage, are essential to successful therapy.

Other Antihypertensive Agents

When INVERSINE is given with other antihypertensive drugs, the dosage of these other agents, as well as that of INVERSINE, should be reduced to avoid excessive hypotension. However, thiazides should be continued in their usual dosage, while that of INVERSINE is decreased by at least 50 percent.

HOW SUPPLIED

Tablets INVERSINE [Inversine ® is a registered trademark of Targacept, Inc. COPYRIGHT© TARGACEPT, INC., 2002 All rights reserved] , 2.5 mg, are slightly yellow, round, compressed tablets, coded LBS01. They are supplied as follows:

NDC 17205-0626-1 in bottles of 100.

STORAGE CONDITION

Store at 25°C (77°F); excursions permitted to 15-30°C (59-86°F)
[see USP Controlled Room [Temperature]

Manufactured by: Siegfried CMS Ltd., Zofingen, Switzerland for Targacept, Inc.
Winston-Salem, NC 27101

Rev.7/02